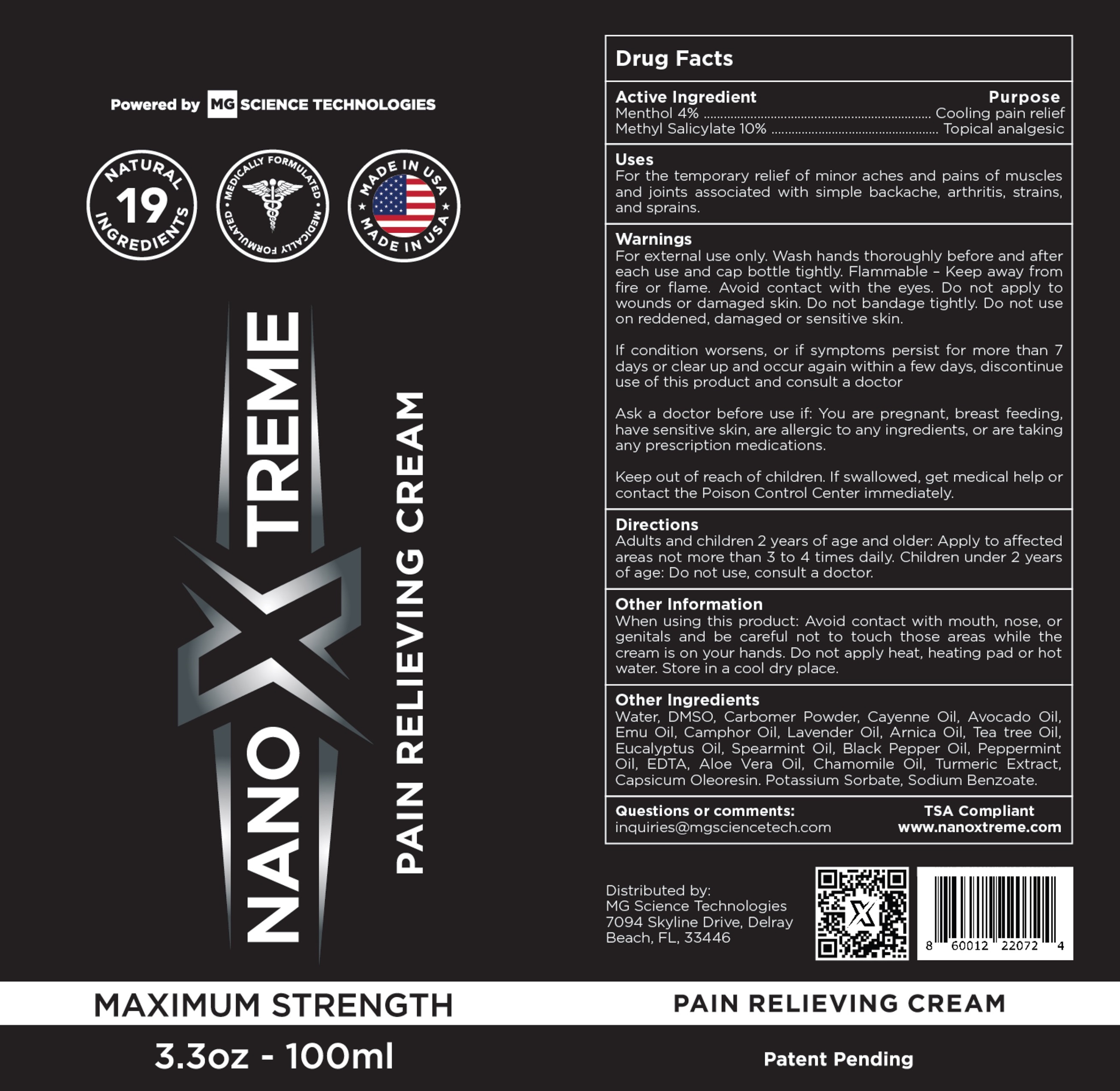 DRUG LABEL: NanoXtreme Pain Relieving
NDC: 84804-321 | Form: CREAM
Manufacturer: MG Science Technologies LLC
Category: otc | Type: HUMAN OTC DRUG LABEL
Date: 20241007

ACTIVE INGREDIENTS: MENTHOL 40 mg/1 mL; METHYL SALICYLATE 100 mg/1 mL
INACTIVE INGREDIENTS: WATER; DIMETHYL SULFOXIDE; AVOCADO OIL; EMU OIL; CAMPHOR OIL; LAVENDER OIL; TEA TREE OIL; EUCALYPTUS OIL; SPEARMINT OIL; BLACK PEPPER OIL; TURMERIC; CAPSICUM OLEORESIN; POTASSIUM SORBATE; SODIUM BENZOATE

NanoXtreme Pain Relieving Cream

Active Ingredient

Menthol 4%

Methyl Salicylate 10%

Purpose

Cooling pain relief

Topical analgesic

Uses

For the temporary relief of minor aches and pains of muscles and joints associated with simple backache, arthritis, strains, and sprains.

Warnings

For external use only. Wash hands thoroughly before and after each use and cap bottle tightly. Flammable - Keep away from fire or flame. Avoid contact with the eyes. Do not apply to wounds or damaged skin. Do not bandage tightly.

Do not use

on reddened, damaged or sensitive skin.

If condition worsens, or if symptoms persist for more than 7 days or clear up and occur again within a few days, discontinue use of this product and consult a doctor

Ask a doctor before use if:

You are pregnant, breast feeding, have sensitive skin, are allergic to any ingredients, or are taking any prescription medications.

Keep out of reach of children.

If swallowed, get medical help or contact the Poison Control Center immediately.

Directions

Adults and children 2 years of age and older: Apply to affected areas not more than 3 to 4 times daily. Children under 2 years of age: Do not use, consult a doctor.

Other Information

When using this product: Avoid contact with mouth, nose, or genitals and be careful not to touch those areas while the cream is on your hands. Do not apply heat, heating pad or hot water. Store in a cool dry place.

Inactive Ingredients

Water, DMSO, Carbomer Powder, Cayenne Oil, Avocado Oil, Emu Oil, Camphor Oil, Lavender Oil, Arnica Oil, Tea tree Oil, Eucalyptus Oil, Spearmint Oil, Black Pepper Oil, Turmeric Extract, Capsicum Oleoresin, Potassium Sorbate, Sodium Benzoate.

Questions or comments:

inquiries@mgsciencetech.com

TSA Compliant

www.nanoxtreme.com